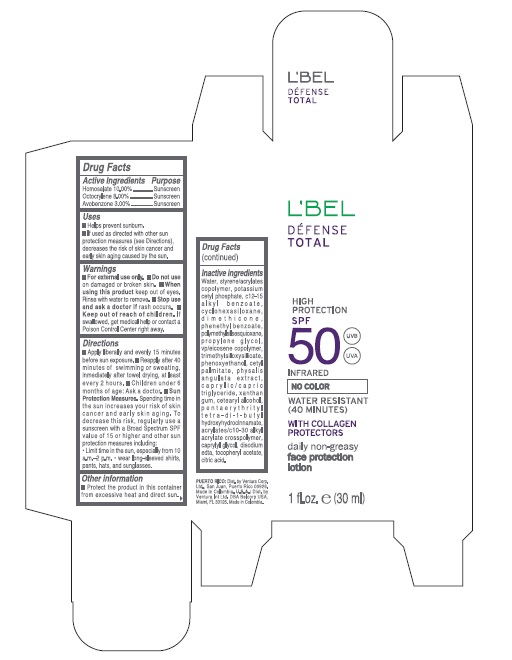 DRUG LABEL: Defense Total High Protection SPF 50 No Color Daily Non-Greasy Face Protection
NDC: 14141-140 | Form: LOTION
Manufacturer: Bel Star S.A. (Colombia)
Category: otc | Type: HUMAN OTC DRUG LABEL
Date: 20241028

ACTIVE INGREDIENTS: OCTOCRYLENE 8 g/100 mL; AVOBENZONE 3 g/100 mL; HOMOSALATE 10 g/100 mL
INACTIVE INGREDIENTS: PENTAERYTHRITOL TETRAKIS(3-(3,5-DI-TERT-BUTYL-4-HYDROXYPHENYL)PROPIONATE); PHENOXYETHANOL; POLYMETHYLSILSESQUIOXANE (4.5 MICRONS); XANTHAN GUM; CETOSTEARYL ALCOHOL; EDETATE DISODIUM ANHYDROUS; PHYSALIS ANGULATA WHOLE; MEDIUM-CHAIN TRIGLYCERIDES; CARBOMER COPOLYMER TYPE B (ALLYL PENTAERYTHRITOL CROSSLINKED); .ALPHA.-TOCOPHEROL ACETATE; CITRIC ACID MONOHYDRATE; CAPRYLYL GLYCOL; PHENETHYL BENZOATE; VINYLPYRROLIDONE/EICOSENE COPOLYMER; POTASSIUM CETYL PHOSPHATE; WATER; ALKYL (C12-15) BENZOATE; PROPYLENE GLYCOL; DIMETHICONE; TRIMETHYLSILOXYSILICATE (M/Q 0.6-0.8); CETYL PALMITATE; CYCLOMETHICONE 6

Defense Total High Protection SPF 50 No Color Daily Non-Greasy Face Protection

Active ingredients

Homosalate 10.00%

Octocrylene 8.00%

Avobenzone 3.00%

Uses

- Helps prevent sunburn
- If used as directed with other sun protection measures (see Directions), decreases the risk of skin cancer and early skin aging caused by the sun.

Warnings

For external use only.

Do not use

on damaged or broken skin

When using this product

keep out of eyes. Rinse with water to remove.

Stop use and ask a doctor if

rash occurs.

Keep out of reach of children.

If product is swallowed, get medical help or contact a Poison Control Center right away

Directions

- Apply liberally and evenly 15 minutes before sun exposure
- Reapply after 40 minutes of swimming or sweating, immediately after towel drying, at least every 2 hours.
- Children under 6 months of age: ask a doctor.
- Sun Protection Measures Spending time in the sun increases your risk of skin cancer and early skin aging. To decrease this risk, regularly use a sunscreen with a Broad Spectrum SPF value of 15 or higher and other sun protection measures including:
- Limit time in the sun, especially from 10 a.m. – 2 p.m.
- wear long-sleeved shirts, pants, hats, and sunglasses

Other information

- Protect the product in this container from excessive heat and direct sun

lnactive ingredients

Water, styrene/acrylates copolymer, potassium cetyl phosphate, c12·15 alkyl benzoate, cyclohexasiloxane, dimethicone, phenethyl benzoate, polymethylsilsesquioxane, propylene glycol, vp/eicosene copolymer, trimethylsiloxysilicate, phenoxyethanol, cetyl palmitate, xanthan gum, physalis angulata extract, caprylic/capric triglyceride, xanthan gum, cetearyl alcohol, pentaerythrityl tetra-di-t-butyl hydroxyhydrocinnamate, acrylates/c10·30 alkyl acrylate crosspolymer, caprylyl glycol, disodium edta, tocopheryl acetate, citric acid

Company Information

PUERTO RICO: Dist. by Ventura Corp. Ltd., San Juan, Puerto Rico 00926.

Made in Colombia.

U.S.A.: Dist. by Ventura Int Ltd. DBA Belcorp USA, Miami, FL 33126.

Purpose

Sunscreen